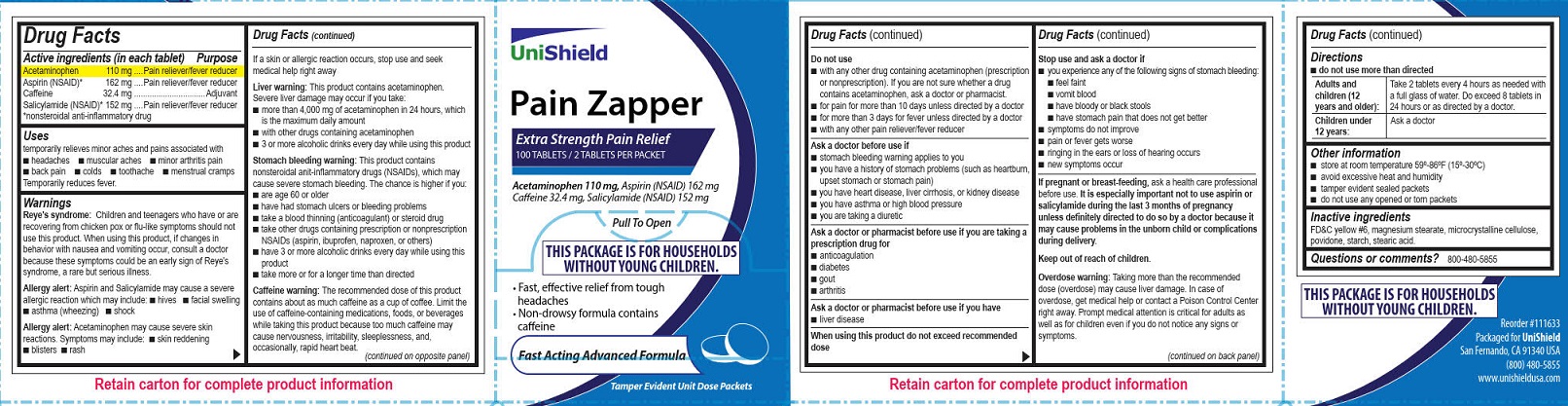 DRUG LABEL: Unishield Pain Zapper
NDC: 49314-8113 | Form: TABLET
Manufacturer: Unishield
Category: otc | Type: HUMAN OTC DRUG LABEL
Date: 20220316

ACTIVE INGREDIENTS: ASPIRIN 162 mg/1 1; SALICYLAMIDE 152 mg/1 1; ACETAMINOPHEN 110 mg/1 1; CAFFEINE 32.4 mg/1 1
INACTIVE INGREDIENTS: MAGNESIUM STEARATE; POVIDONE, UNSPECIFIED; STEARIC ACID; CELLULOSE, MICROCRYSTALLINE; FD&C YELLOW NO. 6; STARCH, CORN

Unishield Pain Zapper

Drug Facts

Active ingredients (in each tablet)

Aspirin (NSAID)* 162 mg

Caffeine 32.4 mg

Salicylamide (NSAID)* 152 mg

*nonsteroidal anti-inflammatory drug

Purpose

Pain reliever/fever reducer

Pain reliever/fever reducer

Adjuvant

Pain reliever/fever reducer

Uses

t emporarily relieved minor aches and pains associated with

■ headaches ■ muscular aches ■ minor arthritis pain ■ back pain ■ colds ■ toothache ■ menstrual cramps

Temporarily reduces fever.

Warnings

Reye's syndrome: Children and teenagers who have or are recovering from chicken pox or flu-like symptoms should not use this product. When using this product, if changes in behavior with nausea and vomiting occur, consult a doctor because these symptoms could be an early sign of Reye's syndrome, a rare but serious illness.

Allergy alert: Aspirin and Salicylamide may cause a severe allergic reaction which may include:

■ hives ■ facial swelling ■ asthma (wheezing) ■ shock

Allergy alert: Acetaminophen may cause severe skin reactions. Symptoms may include:

■ skin reddening ■ blisters ■ rash

If a skin or allergic reaction occurs, stop use and seek medical help right away.

Liver warning: This product contains acetaminophen. Severe liver damage may occur if you take:

■ more than 4,000 mg of acetaminophen in 24 hours, which is the maximum daily amount

■ with other drugs containing acetaminophen

■ 3 or more alcoholic drinks every day while using this product

Stomach bleeding warning: This product contains nonsteroidal anti-inflammatory drugs (NSAIDs), which may cause severe stomach bleeding. The chance is higher if you:

■ are age 60 or older

■ have had stomach ulcers or bleeding problems

■ take a blood thinning (anticoagulant) or steroid drug

■ take other drugs containing prescription or nonprescription NSAIDs (aspirin, ibuprofen, naproxen, or others)

■ have 3 or more alcoholic drinks every day while using this product

■ take more or for a longer time than directed

Caffeine warning: The recommended dose of this product contains about as much caffeine as a cup of coffee. Limit the use of caffeine- containing medications, foods, or beverages while taking this product because too much caffeine may cause nervousness, irritability, sleeplessness, and, occasionally, rapid heart beat

Do not use

■ with any other drug containing acetaminophen (prescription or nonprescription). If you are not sure whether a
drug contains acetaminophen, ask a doctor or pharmacist.

■ for pain for more than 10 days unless directed by a doctor

■for more than 3 days for fever unless directed by a doctor

■ with any other pain reliever/fever reducerl)

Ask a doctor before use if

■ stomach bleeding warning applies to you

■ you have a history of stomach problems (such as heartburn, upset stomach or stomach pain)

■ you have heart disease, liver cirrhosis, or kidney disease

■ you have asthma or high blood pressure

■ you are taking a diuretic

Ask a doctor or pharmacist before use if you are taking a prescription drug for

■ anticoagulation

■ diabetes

■ gout

■ arthritis

Ask a doctor or pharmacist before use if you have

■ liver disease

When using this product do not exceed recommended dose

Stop use and ask a doctor if

■ you experience any of the following signs of stomach bleeding: ■ feel faint ■ vomit blood ■ have bloody or black stools ■ have stomach pain that does not get better

■ symptoms do not improve

■ pain or fever gets worse

■ ringing in the ears or loss of hearing occurs

■ new symptoms occur

PREGNANCY OR BREAST FEEDING

If pregnant or breast-feeding, ask a health care professional before use. It is especially important not to use aspirin and salicylamide during the last 3 months of pregnancy unless definitely directed to do so by a doctor because it may cause problems in the unborn child or complications during delivery.

Keep out of reach of children.

Overdose warning:

Taking more than the recommended dose (overdose) may cause liver damage.

In case of overdose, get medical help or contact a Poison Control Center right away. Prompt medical attention is critical for adults as well as for children even if you do not notice any signs or symptoms.

Directions

■ do not use more than directed

Adults and children(12 years and older): take 2 tablets every 4 hours as needed with a full glass of water. Do not exceed 8 tablets in 24 hours or as directed by a doctor.

Children under 12 years of age: Ask a doctor

Other information

■ store at room temperature 59º-86ºF (15º-30ºC)

■ avoid excessive heat and humidity

■ tamper evident sealed packets

■ do not use any opened or torn packets

Inactive ingredients

FD&C yellow #6, magnesium stearate, microcrystalline cellulose, povidone, starch, stearic acid.

Questions or Comments? 800-480-5855

Unishield Pain Zapper Label

Unishield

Pain Zapper

Extra Strength Pain Relief

100 Tablets/ 2 Tablets Per Packet

Acetaminophen 110 mg. Aspirin (NSAID) 162 mg

Caffeine 32.4 mg. Salicylamide (NSAID) 152 mg

Pull To Open

This Package is for Households wirhout Young Children.

• Fast effective relief from tough headaches

• Non-drowsy formula contains caffeine

Fast Acting Advanced Formula

Tamper Evident Unit Dose Packets